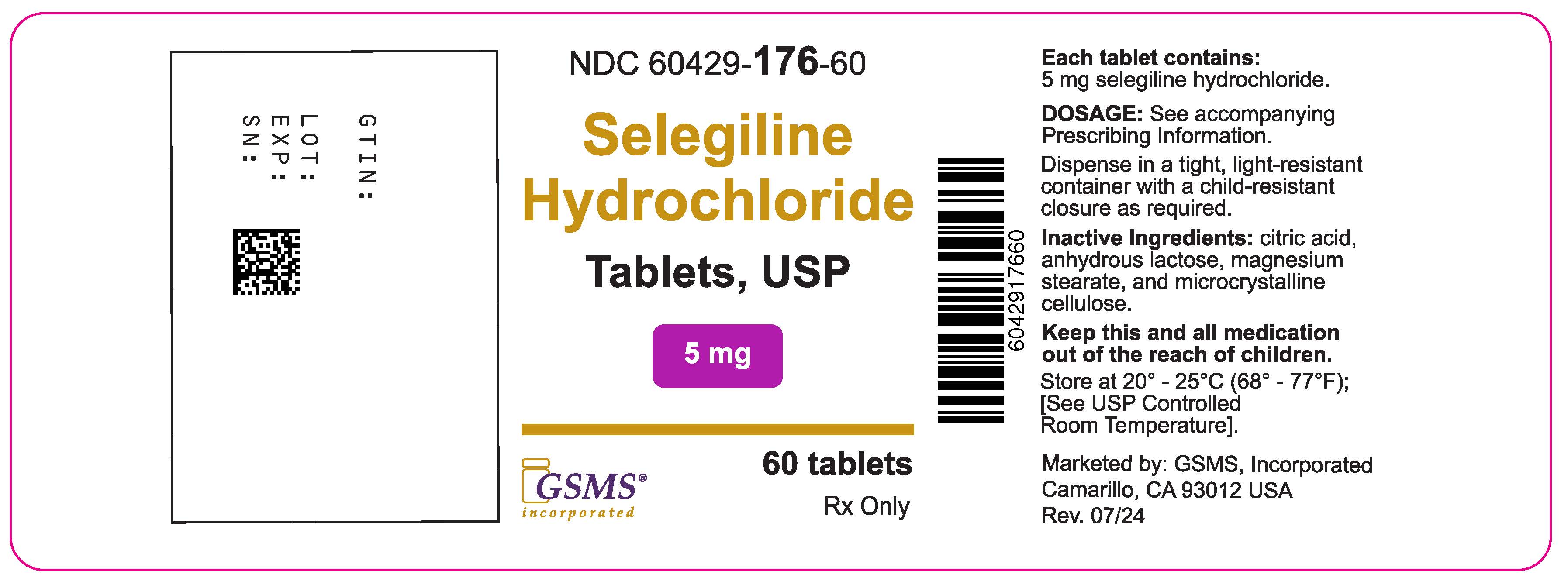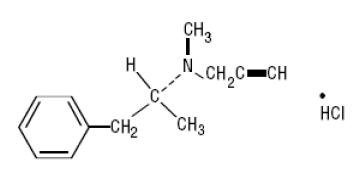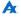 DRUG LABEL: Selegiline Hydrochloride
NDC: 60429-176 | Form: TABLET
Manufacturer: Golden State Medical Supply, Inc.
Category: prescription | Type: HUMAN PRESCRIPTION DRUG LABEL
Date: 20251124

ACTIVE INGREDIENTS: SELEGILINE HYDROCHLORIDE 5 mg/1 1
INACTIVE INGREDIENTS: CITRIC ACID MONOHYDRATE; ANHYDROUS LACTOSE; MAGNESIUM STEARATE; MICROCRYSTALLINE CELLULOSE

Selegiline Hydrochloride Tablets USP 5 mg

DESCRIPTION

Selegiline hydrochloride is a levorotatory acetylenic derivative of phenethylamine. It is commonly referred to in the clinical and pharmacological literature as l-deprenyl.

The chemical name is: (R)-(-)- N,2-dimethyl- N-2-propynylphenethylamine hydrochloride. It is a white to near white crystalline powder, freely soluble in water, chloroform, and methanol, and has a molecular weight of 223.75. The molecular formula is C13H17•HCl. The structural formula is as follows:

Each tablet, for oral administration, contains 5 mg selegiline hydrochloride. Inactive ingredients are citric acid, anhydrous lactose, magnesium stearate, and microcrystalline cellulose.

CLINICAL PHARMACOLOGY

The mechanisms accounting for selegiline's beneficial adjunctive action in the treatment of Parkinson's disease are not fully understood. Inhibition of monoamine oxidase, type B, activity is generally considered to be of primary importance; in addition, there is evidence that selegiline may act through other mechanisms to increase dopaminergic activity.

Selegiline is best known as an irreversible inhibitor of monoamine oxidase (MAO), an intracellular enzyme associated with the outer membrane of mitochondria. Selegiline inhibits MAO by acting as a 'suicide' substrate for the enzyme; that is, it is converted by MAO to an active moiety which combines irreversibly with the active site and/or the enzyme's essential FAD cofactor. Because selegiline has greater affinity for type B rather than for type A active sites, it can serve as a selective inhibitor of MAO type B if it is administered at the recommended dose.

MAOs are widely distributed throughout the body; their concentration is especially high in liver, kidney, stomach, intestinal wall, and brain. MAOs are currently subclassified into two types, A and B, which differ in their substrate specificity and tissue distribution. In humans, intestinal MAO is predominantly type A, while most of that in brain is type B.

In CNS neurons, MAO plays an important role in the catabolism of catecholamines (dopamine, norepinephrine and epinephrine) and serotonin. MAOs are also important in the catabolism of various exogenous amines found in a variety of foods and drugs. MAO in the GI tract and liver (primarily type A), for example, is thought to provide vital protection from exogenous amines (e.g., tyramine) that have the capacity, if absorbed intact, to cause a 'hypertensive crisis,' the so-called 'cheese reaction.' (If large amounts of certain exogenous amines gain access to the systemic circulation - e.g., from fermented cheese, red wine, herring, over-the-counter cough/cold medications, etc. - they are taken up by adrenergic neurons and displace norepinephrine from storage sites within membrane bound vesicles. Subsequent release of the displaced norepinephrine causes the rise in systemic blood pressure, etc.)

In theory, since MAO A of the gut is not inhibited, patients treated with selegiline at a dose of 10 mg a day should be able to take medications containing pharmacologically active amines and consume tyramine-containing foods without risk of uncontrolled hypertension. Although rare, a few reports of hypertensive reactions have occurred in patients receiving selegiline at the recommended dose, with tyramine-containing foods. In addition, one case of hypertensive crisis has been reported in a patient taking the recommended dose of selegiline and a sympathomimetic medication, ephedrine. The pathophysiology of the 'cheese reaction' is complicated and, in addition to its ability to inhibit MAO B selectively, selegiline's relative freedom from this reaction has been attributed to an ability to prevent tyramine and other indirect acting sympathomimetics from displacing norepinephrine from adrenergic neurons. However, until the pathophysiology of the 'cheese reaction' is more completely understood, it seems prudent to assume that selegiline can ordinarily only be used safely without dietary restrictions at doses where it presumably selectively inhibits MAO B (e.g., 10 mg/day).

In short, attention to the dose dependent nature of selegiline's selectivity is critical if it is to be used without elaborate restrictions being placed on diet and concomitant drug use although, as noted above, a few cases of hypertensive reactions have been reported at the recommended dose. (See WARNINGS and PRECAUTIONS.)

It is important to be aware that selegiline may have pharmacological effects unrelated to MAO B inhibition. As noted above, there is some evidence that it may increase dopaminergic activity by other mechanisms, including interfering with dopamine re-uptake at the synapse. Effects resulting from selegiline administration may also be mediated through its metabolites. Two of its three principal metabolites, amphetamine and methamphetamine, have pharmacological actions of their own; they interfere with neuronal uptake and enhance release of several neurotransmitters (e.g., norepinephrine, dopamine, serotonin). However, the extent to which these metabolites contribute to the effects of selegiline are unknown.

Rationale for the Use of a Selective Monoamine Oxidase Type B Inhibitor in Parkinson's Disease

Many of the prominent symptoms of Parkinson's disease are due to a deficiency of striatal dopamine that is the consequence of a progressive degeneration and loss of a population of dopaminergic neurons which originate in the substantia nigra of the midbrain and project to the basal ganglia or striatum. Early in the course of Parkinson's Disease, the deficit in the capacity of these neurons to synthesize dopamine can be overcome by administration of exogenous levodopa, usually given in combination with a peripheral decarboxylase inhibitor (carbidopa).

With the passage of time, due to the progression of the disease and/or the effect of sustained treatment, the efficacy and quality of the therapeutic response to levodopa diminishes. Thus, after several years of levodopa treatment, the response, for a given dose of levodopa, is shorter, has less predictable onset and offset (i.e., there is 'wearing off'), and is often accompanied by side effects (e.g., dyskinesia, akinesias, on-off phenomena, freezing, etc.).

This deteriorating response is currently interpreted as a manifestation of the inability of the ever decreasing population of intact nigrostriatal neurons to synthesize and release adequate amounts of dopamine.

MAO B inhibition may be useful in this setting because, by blocking the catabolism of dopamine, it would increase the net amount of dopamine available (i.e., it would increase the pool of dopamine). Whether or not this mechanism or an alternative one actually accounts for the observed beneficial effects of adjunctive selegiline is unknown.

Selegiline's benefit in Parkinson's disease has only been documented as an adjunct to levodopa/carbidopa. Whether or not it might be effective as a sole treatment is unknown, but past attempts to treat Parkinson's disease with nonselective MAOI monotherapy are reported to have been unsuccessful. It is important to note that attempts to treat Parkinsonian patients with combinations of levodopa and currently marketed non-selective MAO inhibitors were abandoned because of multiple side effects including hypertension, increase in involuntary movement and toxic delirium.

Pharmacokinetic Information (Absorption, Distribution, Metabolism and Elimination - ADME)

The absolute bioavailability of selegiline following oral dosing is not known; however, selegiline undergoes extensive metabolism (presumably attributable to presystemic clearance in gut and liver). The major plasma metabolites are N-desmethylselegiline, L-amphetamine and L-methamphetamine. Only N-desmethylselegiline has MAO-B inhibiting activity. The peak plasma levels of these metabolites following a single oral dose of 10 mg are from 4 to almost 20 times greater than that of the maximum plasma concentration of selegiline (1 ng/mL). The maximum concentrations of amphetamine and methamphetamine, however, are far below those ordinarily expected to produce clinically important effects.

Single oral dose studies do not predict multiple dose kinetics, however, at steady state the peak plasma level of selegiline is 4 fold that obtained following a single dose. Metabolite concentrations increase to a lesser extent, averaging 2 fold that seen after a single dose.

The bioavailability of selegiline is increased 3 to 4 fold when it is taken with food.

The extent of systemic exposure to selegiline at a given dose varies considerably among individuals. Estimates of systemic clearance of selegiline are not available. Following a single oral dose, the mean elimination half-life of selegiline is two hours. Under steady state conditions the elimination half-life increases to ten hours.

Because selegiline's inhibition of MAO-B is irreversible, it is impossible to predict the extent of MAO-B inhibition from steady state plasma levels. For the same reason, it is not possible to predict the rate of recovery of MAO-B activity as a function of plasma levels. The recovery of MAO-B activity is a function of de novo protein synthesis; however, information about the rate of de novo protein synthesis is not yet available. Although platelet MAO-B activity returns to the normal range within 5 to 7 days of selegiline discontinuation, the linkage between platelet and brain MAO-B inhibition is not fully understood nor is the relationship of MAO-B inhibition to the clinical effect established (see CLINICAL PHARMACOLOGY).

Special Populations

Renal Impairment

No pharmacokinetic information is available on selegiline or its metabolites in renally impaired subjects.

Hepatic Impairment

No pharmacokinetic information is available on selegiline or its metabolites in hepatically impaired subjects.

Age

Although a general conclusion about the effects of age on the pharmacokinetics of selegiline is not warranted because of the size of the sample evaluated (12 subjects greater than 60 years of age, 12 subjects between the ages of 18 to 30), systemic exposure was about twice as great in older as compared to a younger population given a single oral dose of 10 mg.

Gender

No information is available on the effects of gender on the pharmacokinetics of selegiline.

INDICATIONS AND USAGE

Selegiline Hydrochloride Tablets USP are indicated as an adjunct in the management of Parkinsonian patients being treated with levodopa/carbidopa who exhibit deterioration in the quality of their response to this therapy. There is no evidence from controlled studies that selegiline has any beneficial effect in the absence of concurrent levodopa therapy.

Evidence supporting this claim was obtained in randomized controlled clinical investigations that compared the effects of added selegiline or placebo in patients receiving levodopa/carbidopa. Selegiline was significantly superior to placebo on all three principal outcome measures employed: change from baseline in daily levodopa/carbidopa dose, the amount of 'off' time, and patient self-rating of treatment success. Beneficial effects were also observed on other measures of treatment success (e.g., measures of reduced end of dose akinesia, decreased tremor and sialorrhea, improved speech and dressing ability and improved overall disability as assessed by walking and comparison to previous state).

CONTRAINDICATIONS

Selegiline hydrochloride is contraindicated in patients with a known hypersensitivity to this drug.

Selegiline is contraindicated for use with meperidine. This contraindication is often extended to other opioids. (See Drug Interactions.)

WARNINGS

Selegiline should not be used at daily doses exceeding those recommended (10 mg/day) because of the risks associated with non-selective inhibition of MAO. (See CLINICAL PHARMACOLOGY.)

The selectivity of selegiline for MAO B may not be absolute even at the recommended daily dose of 10 mg a day. Rare cases of hypertensive reactions associated with ingestion of tyramine-containing foods have been reported in patients taking the recommended daily dose of selegiline. The selectivity is further diminished with increasing daily doses. The precise dose at which selegiline becomes a non-selective inhibitor of all MAO is unknown, but may be in the range of 30 to 40 mg a day.

Severe CNS toxicity associated with hyperpyrexia and death have been reported with the combination of tricyclic antidepressants and non-selective MAOIs (Phenelzine, Tranylcypromine). A similar reaction has been reported for a patient on amitriptyline and selegiline. Another patient receiving protriptyline and selegiline developed tremors, agitation, and restlessness followed by unresponsiveness and death two weeks after selegiline was added. Related adverse events including hypertension, syncope, asystole, diaphoresis, seizures, changes in behavioral and mental status, and muscular rigidity have also been reported in some patients receiving selegiline and various tricyclic antidepressants.

Serious, sometimes fatal, reactions with signs and symptoms that may include hyperthermia, rigidity, myoclonus, autonomic instability with rapid fluctuations of the vital signs, and mental status changes that include extreme agitation progressing to delirium and coma have been reported with patients receiving a combination of fluoxetine hydrochloride and non-selective MAOIs. Similar signs have been reported in some patients on the combination of selegiline (10 mg a day) and selective serotonin reuptake inhibitors including fluoxetine, sertraline and paroxetine.

Since the mechanisms of these reactions are not fully understood, it seems prudent, in general, to avoid this combination of selegiline and tricyclic antidepressants as well as selegiline and selective serotonin reuptake inhibitors. At least 14 days should elapse between discontinuation of selegiline and initiation of treatment with a tricyclic antidepressant or selective serotonin reuptake inhibitors. Because of the long half lives of fluoxetine and its active metabolite, at least five weeks (perhaps longer, especially if fluoxetine has been prescribed chronically and/or at higher doses) should elapse between discontinuation of fluoxetine and initiation of treatment with selegiline.

PRECAUTIONS

General

Some patients given selegiline may experience an exacerbation of levodopa associated side effects, presumably due to the increased amounts of dopamine reaction with super sensitive, post-synaptic receptors. These effects may often be mitigated by reducing the dose of levodopa/carbidopa by approximately 10 to 30%.

The decision to prescribe selegiline should take into consideration that the MAO system of enzymes is complex and incompletely understood and there is only a limited amount of carefully documented clinical experience with selegiline. Consequently, the full spectrum of possible responses to selegiline may not have been observed in pre-marketing evaluation of the drug. It is advisable, therefore, to observe patients closely for atypical responses.

Melanoma

Epidemiological studies have shown that patients with Parkinson's disease have a higher risk (2-to approximately 6-fold higher) of developing melanoma than the general population. Whether the increased risk observed was due to Parkinson's disease or other factors, such as drugs used to treat Parkinson's disease, is unclear. For the reasons stated above, patients and providers are advised to monitor for melanomas frequently and on a regular basis when using selegiline for any indication. Ideally, periodic skin examinations should be performed by appropriately qualified individuals (e.g., dermatologists).

Information for Patients

Patients should be advised of the possible need to reduce levodopa dosage after the initiation of selegiline therapy.

Patients (or their families if the patient is incompetent) should be advised not to exceed the daily recommended dose of 10 mg. The risk of using higher daily doses of selegiline should be explained, and a brief description of the 'cheese reaction' provided. Rare hypertensive reactions with selegiline at recommended doses associated with dietary influences have been reported.

Consequently, it may be useful to inform patients (or their families) about the signs and symptoms associated with MAOI induced hypertensive reactions. In particular, patients should be urged to report, immediately, any severe headache or other atypical or unusual symptoms not previously experienced.

There have been reports of patients experiencing intense urges to gamble, increased sexual urges, and other intense urges and the inability to control these urges while taking one or more of the medications that increase central dopaminergic tone, that are generally used for the treatment of Parkinson’s disease, including selegiline. Although it is not proven that the medications caused these events, these urges were reported to have stopped in some cases when the dose was reduced or the medication was stopped. Prescribers should ask patients about the development of new or increased gambling urges, sexual urges or other urges while being treated with selegiline. Patients should inform their physician if they experience new or increased gambling urges, increased sexual urges or other intense urges while taking selegiline. Physicians should consider dose reduction or stopping the medication if a patient develops such urges while taking selegiline.

Laboratory Tests

No specific laboratory tests are deemed essential for the management of patients on selegiline. Periodic routine evaluation of all patients, however, is appropriate.

Drug Interactions

The occurrence of stupor, muscular rigidity, severe agitation, and elevated temperature has been reported in some patients receiving the combination of selegiline and meperidine. Symptoms usually resolve over days when the combination is discontinued. This is typical of the interaction of meperidine and MAOIs. Other serious reactions (including severe agitation, hallucinations, and death) have been reported in patients receiving this combination (see CONTRAINDICATIONS). Severe toxicity has also been reported in patients receiving the combination of tricyclic antidepressants and selegiline and selective serotonin reuptake inhibitors and selegiline. (See WARNINGSfor details.) One case of hypertensive crisis has been reported in a patient taking the recommended doses of selegiline and a sympathomimetic medication (ephedrine).

Carcinogenesis, Mutagenesis, and Impairment of Fertility

Assessment of the carcinogenic potential of selegiline in mice and rats is ongoing for all dosage forms. Selegiline did not induce mutations or chromosomal damage when tested in the bacterial mutation assay in Salmonella typhimurium and in an in vivo chromosomal aberration assay. While these studies provide some reassurance that selegiline is not mutagenic or clastogenic, they are not definitive because of methodological limitations. No definitive in vitro chromosomal aberration or in vitro mammalian gene mutation assays have been performed.

The effect of selegiline on fertility has not been adequately assessed.

Pregnancy

Pregnancy Category C

No teratogenic effects were observed in a study of embryo-fetal development in Sprague-Dawley rats at oral doses of 4, 12, and 36 mg/kg or 4, 12 and 35 times the human therapeutic dose on a mg/m^2basis. No teratogenic effects were observed in a study of embryo-fetal development in New Zealand White rabbits at oral doses of 5, 25, and 50 mg/kg or 10, 48, and 95 times the human therapeutic dose on a mg/m^2basis; however, in this study, the number of litters produced at the two higher doses was less than recommended for assessing teratogenic potential. In the rat study, there was a decrease in fetal body weight at the highest dose tested. In the rabbit study, increases in total resorptions and % post-implantation loss, and a decrease in the number of live fetuses per dam occurred at the highest dose tested. In a peri- and postnatal development study in Sprague-Dawley rats (oral doses of 4, 16, and 64 mg/kg or 4, 15, and 62 times the human therapeutic dose on a mg/m^2basis), an increase in the number of stillbirths and decreases in the number of pups per dam, pup survival, and pup body weight (at birth and throughout the lactation period) were observed at the two highest doses. At the highest dose tested, no pups born alive survived to Day 4 postpartum. Postnatal development at the highest dose tested in dams could not be evaluated because of the lack of surviving pups. The reproductive performance of the untreated offspring was not assessed.

There are no adequate and well-controlled studies in pregnant women. Selegiline should be used during pregnancy only if the potential benefit justifies the potential risk to the fetus.

Nursing Mothers

It is not known whether selegiline hydrochloride is excreted in human milk. Because many drugs are excreted in human milk, consideration should be given to discontinuing the use of all but absolutely essential drug treatments in nursing women.

Pediatric Use

The effects of selegiline hydrochloride in children have not been evaluated.

ADVERSE REACTIONS

Introduction

The number of patients who received selegiline in prospectively monitored pre-marketing studies is limited. While other sources of information about the use of selegiline are available (e.g., literature reports, foreign post-marketing reports, etc.) they do not provide the kind of information necessary to estimate the incidence of adverse events. Thus, overall incidence figures for adverse reactions associated with the use of selegiline cannot be provided. Many of the adverse reactions seen have also been reported as symptoms of dopamine excess.

Moreover, the importance and severity of various reactions reported often cannot be ascertained. One index of relative importance, however, is whether or not a reaction caused treatment discontinuation. In prospective pre-marketing studies, the following events led, in decreasing order of frequency, to discontinuation of treatment with selegiline: nausea, hallucinations, confusion, depression, loss of balance, insomnia, orthostatic hypotension, increased akinetic involuntary movements, agitation, arrhythmia, bradykinesia, chorea, delusions, hypertension, new or increased angina pectoris and syncope. Events reported only once as a cause of discontinuation are ankle edema, anxiety, burning lips/mouth, constipation, drowsiness/lethargy, dystonia, excess perspiration, increased freezing, gastrointestinal bleeding, hair loss, increased tremor, nervousness, weakness and weight loss.

Experience with selegiline obtained in parallel, placebo controlled, randomized studies provides only a limited basis for estimates of adverse reaction rates. The following reactions that occurred with greater frequency among the 49 patients assigned to selegiline as compared to the 50 patients assigned to placebo in the only parallel, placebo controlled trial performed in patients with Parkinson's disease are shown in the following Table. None of these adverse reactions led to a discontinuation of treatment.

INCIDENCE OF TREATMENT-EMERGENT ADVERSE EXPERIENCES IN THE PLACEBO-CONTROLLED CLINICAL TRIAL
Adverse Event | Number of Patients Reporting Events
 | selegiline hydrochloride N = 49 | placebo N = 50
Nausea | 10 | 3
Dizziness/Light-headed/Fainting | 7 | 1
Abdominal Pain | 4 | 2
Confusion | 3 | 0
Hallucinations | 3 | 1
Dry mouth | 3 | 1
Vivid Dreams | 2 | 0
Dyskinesias | 2 | 5
Headache | 2 | 1
The following events were reported once in either or both groups:
Ache, generalized | 1 | 0
Anxiety/Tension | 1 | 1
Anemia | 0 | 1
Diarrhea | 1 | 0
Hair Loss | 0 | 1
Insomnia | 1 | 1
Lethargy | 1 | 0
Leg pain | 1 | 0
Low back pain | 1 | 0
Malaise | 0 | 1
Palpitations | 1 | 0
Urinary Retention | 1 | 0
Weight Loss | 1 | 0

In all prospectively monitored clinical investigations, enrolling approximately 920 patients, the following adverse events, classified by body system, were reported.

Central Nervous System

Motor/Coordination/Extrapyramidal

increased tremor, chorea, loss of balance, restlessness, blepharospasm, increased bradykinesia, facial grimace, falling down, heavy leg, muscle twitch*, myoclonic jerks*, stiff neck, tardive dyskinesia, dystonic symptoms, dyskinesia, involuntary movements, freezing, festination, increased apraxia, muscle cramps.

Mental Status/Behavioral/Psychiatric

hallucinations, dizziness, confusion, anxiety, depression, drowsiness, behavior/mood change, dreams/nightmares, tiredness, delusions, disorientation, lightheadedness, impaired memory*, increased energy*, transient high*, hollow feeling, lethargy/malaise, apathy, overstimulation, vertigo, personality change, sleep disturbance, restlessness, weakness, transient irritability.

Pain/Altered Sensation

headache, back pain, leg pain, tinnitus, migraine, supraorbital pain, throat burning, generalized ache, chills, numbness of toes/fingers, taste disturbance.

Autonomic Nervous System

dry mouth, blurred vision, sexual dysfunction.

Cardiovascular

orthostatic hypotension, hypertension, arrhythmia, palpitations, new or increased angina pectoris, hypotension, tachycardia, peripheral edema, sinus bradycardia, syncope.

Gastrointestinal

nausea/vomiting, constipation, weight loss, anorexia, poor appetite, dysphagia, diarrhea, heartburn, rectal bleeding, bruxism*, gastrointestinal bleeding (exacerbation of preexisting ulcer disease).

Genitourinary/Gynecologic/Endocrine

slow urination, transient anorgasmia*, nocturia, prostatic hypertrophy, urinary hesitancy, urinary retention, decreased penile sensation*, urinary frequency.

*Indicates events reported only at doses greater than 10 mg/day.

Skin and Appendages

increased sweating, diaphoresis, facial hair, hair loss, hematoma, rash, photosensitivity.

Miscellaneous

asthma, diplopia, shortness of breath, speech affected.

Postmarketing Reports

The following experiences were described in spontaneous post-marketing reports. These reports do not provide sufficient information to establish a clear causal relationship with the use of selegiline hydrochloride.

CNS

Seizure in dialyzed chronic renal failure patient on concomitant medications.

OVERDOSAGE

Selegiline

No specific information is available about clinically significant overdoses with selegiline hydrochloride. However, experience gained during selegiline's development reveals that some individuals exposed to doses of 600 mg of d,l-selegiline suffered severe hypotension and psychomotor agitation.

Since the selective inhibition of MAO B by selegiline hydrochloride is achieved only at doses in the range recommended for the treatment of Parkinson's disease (e.g., 10 mg/day), overdoses are likely to cause significant inhibition of both MAO A and MAO B. Consequently, the signs and symptoms of overdose may resemble those observed with marketed non-selective MAO inhibitors (e.g., tranylcypromine, isocarboxazide, and phenelzine).

Overdose with Non-Selective MAO Inhibition

NOTE:This section is provided for reference; it does not describe events that have actually been observed with selegiline in overdose.

Characteristically, signs and symptoms of non-selective MAOI overdose may not appear immediately. Delays of up to 12 hours between ingestion of drug and the appearance of signs may occur. Importantly, the peak intensity of the syndrome may not be reached for upwards of a day following the overdose. Death has been reported following overdosage. Therefore, immediate hospitalization, with continuous patient observation and monitoring for a period of at least two days following the ingestion of such drugs in overdose, is strongly recommended.

The clinical picture of MAOI overdose varies considerably; its severity may be a function of the amount of drug consumed. The central nervous and cardiovascular systems are prominently involved.

Signs and symptoms of overdosage may include, alone or in combination, any of the following: drowsiness, dizziness, faintness, irritability, hyperactivity, agitation, severe headache, hallucinations, trismus, opisthotonus, convulsions, and coma; rapid and irregular pulse, hypertension, hypotension and vascular collapse; precordial pain, respiratory depression and failure, hyperpyrexia, diaphoresis, and cool, clammy skin.

Treatment Suggestions for Overdose

NOTE: Because there is no recorded experience with selegiline overdose, the following suggestions are offered based upon the assumption that selegiline overdose may be modeled by non-selective MAOI poisoning. In any case, up-to-date information about the treatment of overdose can often be obtained from a certified Regional Poison Control Center. Telephone numbers of certified Poison Control Centers are listed in the Physicians' Desk Reference (PDR).

Treatment of overdose with non-selective MAOIs is symptomatic and supportive. Induction of emesis or gastric lavage with instillation of charcoal slurry may be helpful in early poisoning, provided the airway has been protected against aspiration. Signs and symptoms of central nervous system stimulation, including convulsions, should be treated with diazepam, given slowly intravenously. Phenothiazine derivatives and central nervous system stimulants should be avoided. Hypotension and vascular collapse should be treated with intravenous fluids and, if necessary, blood pressure titration with an intravenous infusion of a dilute pressor agent. It should be noted that adrenergic agents may produce a markedly increased pressor response.

Respiration should be supported by appropriate measures, including management of the airway, use of supplemental oxygen, and mechanical ventilatory assistance, as required.

Body temperature should be monitored closely. Intensive management of hyperpyrexia may be required. Maintenance of fluid and electrolyte balance is essential.

DOSAGE AND ADMINISTRATION

Selegiline hydrochloride tablets USP are intended for administration to Parkinsonian patients receiving levodopa/carbidopa therapy who demonstrate a deteriorating response to this treatment. The recommended regimen for the administration of Selegiline Hydrochloride Tablets USP is 10 mg per day administered as divided doses of 5 mg each taken at breakfast and lunch. There is no evidence that additional benefit will be obtained from the administration of higher doses. Moreover, higher doses should ordinarily be avoided because of the increased risk of side effects.

After two to three days of selegiline treatment, an attempt may be made to reduce the dose of levodopa/carbidopa. A reduction of 10 to 30% was achieved with the typical participant in the domestic placebo controlled trials who was assigned to selegiline treatment. Further reductions of levodopa/carbidopa may be possible during continued selegiline therapy.

HOW SUPPLIED

Selegiline Hydrochloride Tablets USP 5 mg are available for oral administration as white or slightly mottled, round, unscored tablets imprinted with on one side and “3438” on the other side. They are supplied as bottles of 60 (NDC 60429-176-60).

Storage
Store at 20° to 25°C (68° to 77°F) [see USP Controlled Room Temperature].

Dispense in a tight, light-resistant container [see USP] with a child-resistant closure as required.

APOTEX INC.
SELEGILINE HYDROCHLORIDE TABLETS USP
5 mg

Manufactured by: Manufactured for:
Apotex Inc. Apotex Corp.
Toronto, Ontario Weston, Florida
Canada M9L 1T9 33326

Revised: June 2009

Rev. 1

Marketed by:
GSMS, Inc.
Camarillo, CA 93012 USA

PRINCIPAL DISPLAY PANEL-5 mg BOTTLE LABEL

Representative sample of labeling (see HOW SUPPLIEDsection for completed listing):

NDC 60429-176-60

SELEGILINE HYDROCHLORIDE TABLETS USP

5 mg

Rx Only

60 Tablets